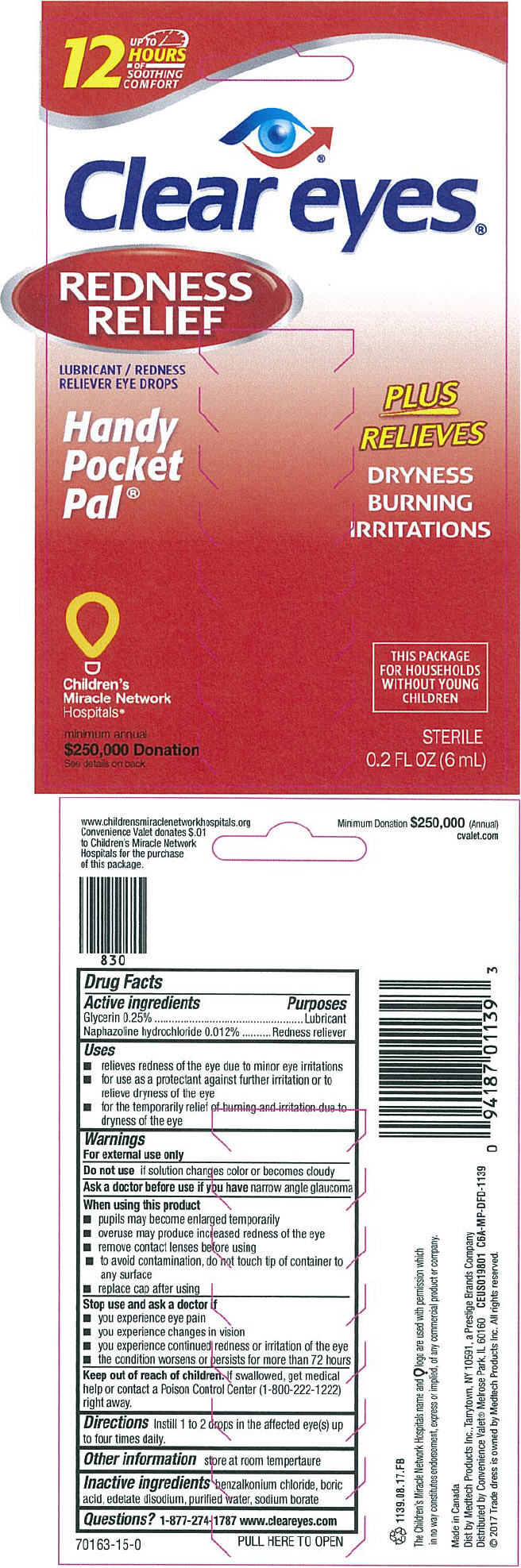 DRUG LABEL: CLEAR EYES REDNESS RELIEF HANDY POCKET PAL
NDC: 29485-1139 | Form: SOLUTION/ DROPS
Manufacturer: Mechanical Servants LLC
Category: otc | Type: HUMAN OTC DRUG LABEL
Date: 20180718

ACTIVE INGREDIENTS: NAPHAZOLINE HYDROCHLORIDE 0.00012 mg/1 mL; GLYCERIN 0.0025 mg/1 mL
INACTIVE INGREDIENTS: BENZALKONIUM CHLORIDE; BORIC ACID; EDETATE DISODIUM; WATER; SODIUM BORATE

CLEAR EYES® REDNESS RELIEF HANDY POCKET PAL®

Drug Facts

ACTIVE INGREDIENT

PURPOSE

Active ingredients | Purposes
Glycerin 0.25% | Lubricant
Naphazoline hydrochloride 0.012% | Redness reliever

Uses

- relieves redness of the eye due to minor eye irritations
- for use as a protectant against further irritation or to relieve dryness of the eye
- for the temporarily relief of burning and irritation due to dryness of the eye

Warnings

For external use only

Do not use if solution changes color or becomes cloudy

Ask a doctor before use if you have narrow angle glaucoma

When using this product

- pupils may become enlarged temporarily
- overuse may produce increased redness of the eye
- remove contact lenses before using
- to avoid contamination, do not touch tip of container to any surface
- replace cap after using

Stop use and ask doctor if

- you experience eye pain
- you experience changes in vision
- you experience continued redness or irritation of the eye
- the condition worsens or persists for more than 72 hours

Keep out of reach of children. If swallowed, get medical help or contact a Poison Control Center (1-800-222-1222) right away.

Directions

Instill 1 to 2 drops in the affected eye(s) up to four times daily.

Other information

store at room temperature

Inactive ingredients

benzalkonium chloride, boric acid, edetate disodium, purified water, sodium borate

Questions?

1-877-274-1787 www.cleareyes.com

Dist by Medtech Products Inc., Tarrytown, NY 10591, a Prestige Brands Company
Distributed by Convenience Valet® Melrose Park, IL 60160

PRINCIPAL DISPLAY PANEL - 6 mL Bottle Box

UP TO
12
HOURS
OF
SOOTHING
COMFORT

Clear eyes®

REDNESS
RELIEF

LUBRICANT / REDNESS
RELIEVER EYE DROPS

Handy
Pocket
Pal®

PLUS
RELIEVES

DRYNESS
BURNING
IRRITATIONS

Children's
Miracle Network
Hospitals®

minimum annual
$250,000 Donation
See details on back

THIS PACKAGE
FOR HOUSEHOLDS
WITHOUT YOUNG
CHILDREN

STERILE
0.2 FL OZ (6 mL)